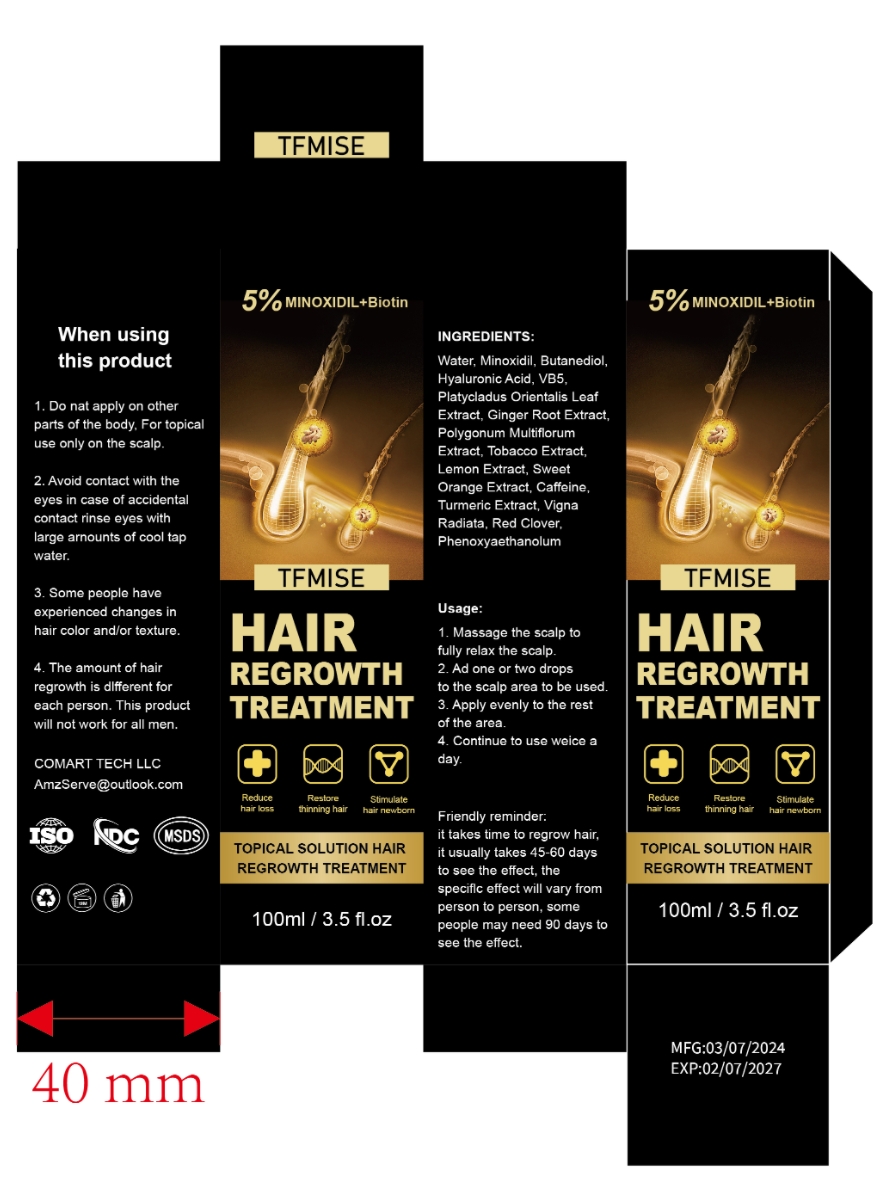 DRUG LABEL: TFMISE HAIR REGROWTH TREATMENT
NDC: 84542-367 | Form: LIQUID
Manufacturer: COMART TECH LLC
Category: otc | Type: HUMAN OTC DRUG LABEL
Date: 20240722

ACTIVE INGREDIENTS: MINOXIDIL 5 g/100 mL
INACTIVE INGREDIENTS: WATER; HYALURONIC ACID; PANTHENOL; RED CLOVER; BIOTIN; CAFFEINE; PHENOXYETHANOL

ACTIVE INGREDIENTS

MINOXIDIL 5%

PURPOSE

Reduce Hair Loss
Restore thinning hair
Stimulate hair newborn

Keep it away from children and pets

Usage:

1. Massage the scalp to fully relax the scalp.

2. Ad one or two drops to the scalp area to be used.

3. Apply evenly to the rest of the area.

4. Continue to use weice a day.

WARNINGS

External use only.

DOSAGE AND ADMINISTRATION

Twice each day, 4 sprays (1ml)each time. 50 days supply

STORAGE AND HANDLING

Store in a cool place

INACTIVE INGREDIENT

water、butanediol、hyaluronic acid、VB5、Platycladus orientalis leaf extract、Ginger root extract、Polygonum multiflorum extract、Tobacco extract、lemon extract、Sweet orange extract、caffeine、Turmeric extract、vigna radiata、red clover、phenoxyaethanolum

DO NOT USE

You have no family history of hair loss,hair loss is sudden and/or patchy.
You do not know the reason for you hair loss.
You ae under 18 years of age, Do not use it on babies and children your scalp is red,inflamed,infected, irritated, or painful.
You use other medicines on the scalp.Ask a doctor before use if you hace heart disease.

PACKAGE LABEL

INGREDIENTS:Water,biotin, Minoxidil, Butanediol, Hyaluronic Acid, VB5, Platycladus Orientalis Leaf Extract, Ginger Root Extract,Polygonum MultiflorumExtract, Tobacco Extract, Lemon Extract, Sweet Orange Extract, Caffeine, Turmeric Extract, Vigna Radiata, Red Clover,Phenoxyaethanolum

Usage:

1. Massage the scalp to fully relax the scalp.

2. Ad one or two drops to the scalp area to be used.

3. Apply evenly to the rest of the area.

4. Continue to use weice a day.

When using this product

1. Do not apply on other parts of the body, For topical use only on the scalp.

2. Avoid contact with the eyes in case of accidental contact rinse eyes with large arnounts of cool tap water.

3. Some people have experienced changes in hair color and/or texture.

4. The amount of hair regrowth is dlfferent for each person. This product will not work for all men.

Usage:1. Massage the scalp to fully relax the scalp.2. Ad one or two dropsto the scalp area to be used.3. Apply evenly to the rest of the area.4. Continue to use weice a day.

Friendly reminder: it takes time to regrow hair, it usually takes 45-60 days to see the effect, the speciflc effect will vary from person to person, some people may need 90 days to see the effect.